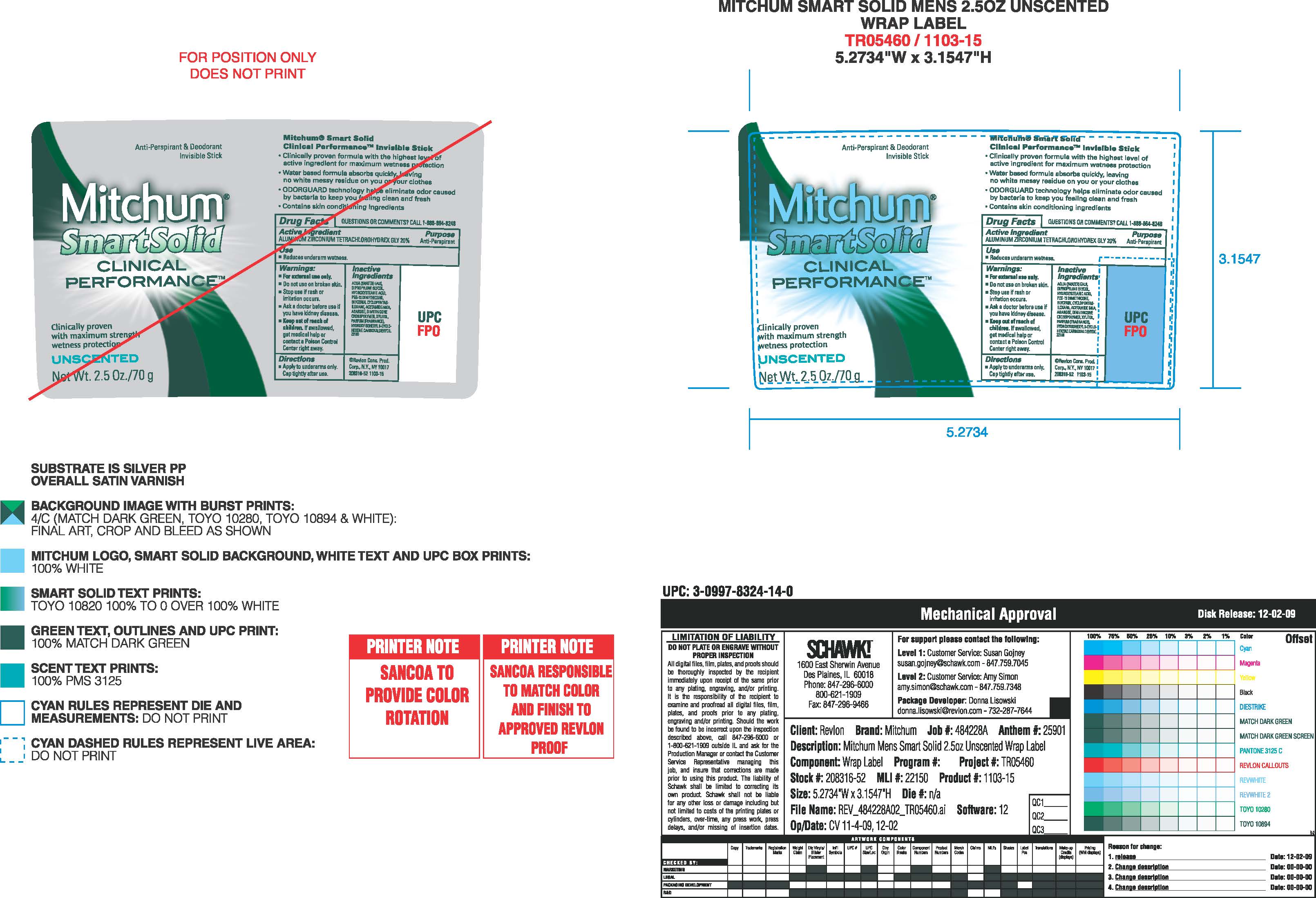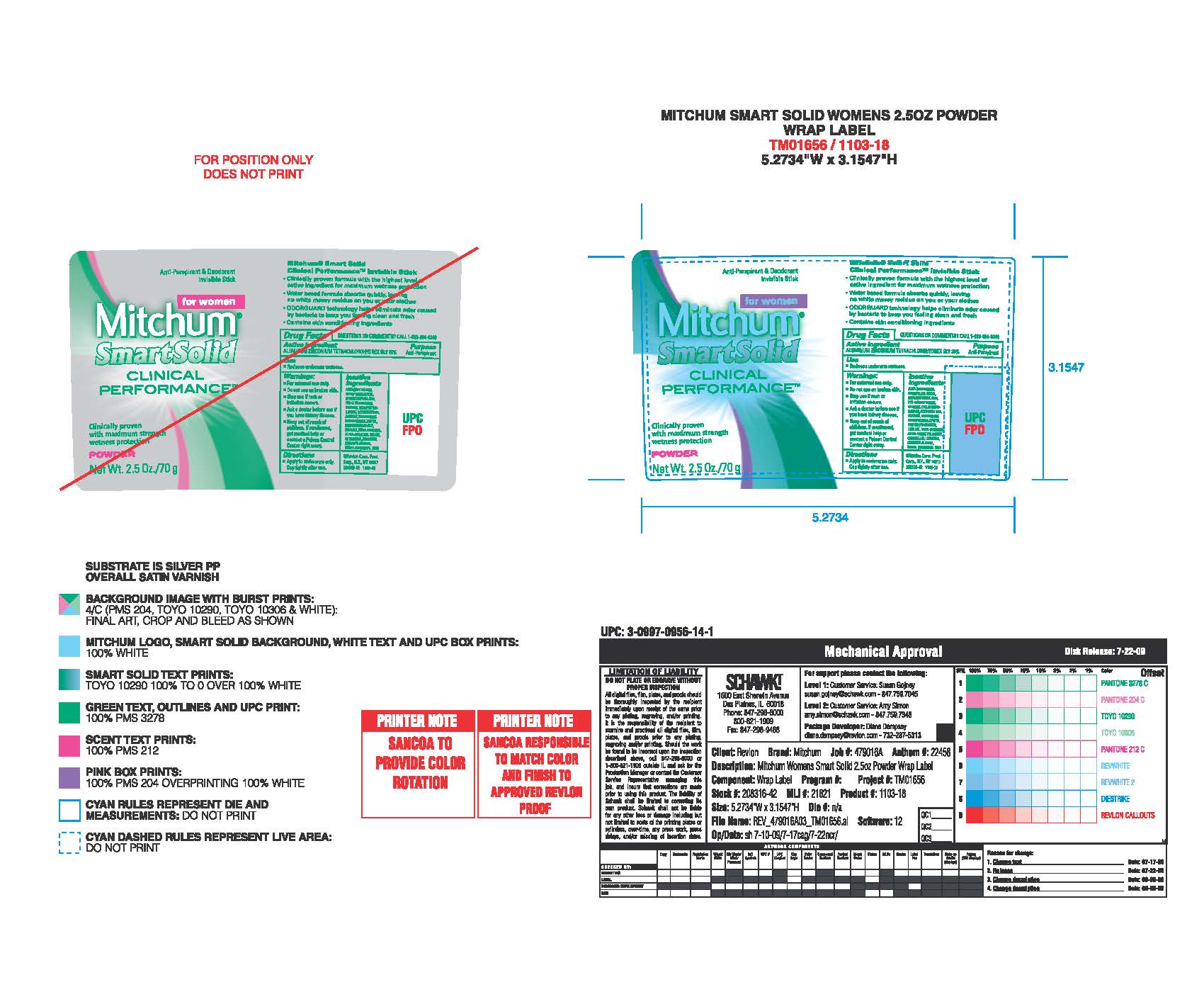 DRUG LABEL: Mitchum Smart Solid
NDC: 10967-613 | Form: LIQUID
Manufacturer: Revlon Consumer Products Corp
Category: otc | Type: HUMAN OTC DRUG LABEL
Date: 20240112

ACTIVE INGREDIENTS: ALUMINUM ZIRCONIUM TETRACHLOROHYDREX GLY 0.2 g/1 mL
INACTIVE INGREDIENTS: .BETA.-CITRONELLOL, (R)-; GERANIOL; LIMONENE, (+/-)-; LINALOOL, (+/-)-; WATER; DIPROPYLENE GLYCOL; 12-HYDROXYSTEARIC ACID; PEG-12 DIMETHICONE; GLYCERIN; CYCLOHEXYL CINNAMATE; ISOMETHYL-.ALPHA.-IONONE; XYLITOL; CINNAMYL ALCOHOL; BENZYL CINNAMATE; CYCLOMETHICONE 5; ACETIC MONOETHANOLAMIDE

Mitchum Smart Solid

ACTIVE INGREDIENT

Aluminum Zirconium Tetrachlorohydrex Gly 20%

Purpose

Antiperspirant

Warnings:

For external use only.

Do not use on broken skin

Ask a doctor before use if you have kidney disease

Stop use if rash or irriation occurs

KEEP OUT OF REACH OF CHILDREN

If swallowed, get medical help or contact a Poison Control Center right away.

Inactive Ingredients

AQUA ((WATER) EAU), DIPROPYLENE GLYCOL, HYDROXYSTEARIC ACID, PEG-12 DIMETHICONE, GLYCERIN, CYCLOPENTASILOXANE, PARFUM (FRAGRANCE), ACETAMIDE MEA, AGAROSE, DIMETHICONE CROSSPOLYMER, LINALOOL, HEXYL CINNAMAL, ALPHA-ISOMETHYL IONONE, XYLITOL, CITRONELLOL, LIMONENE, CINNAMYL ALCOHOL, BENZYL CINNAMATE

INDICATIONS AND USAGE

Reduces underarm wetness

PACKAGE LABEL

Mitchum Smart Solid

Clinical Performance

Net wt. 2.5oz/ 70g